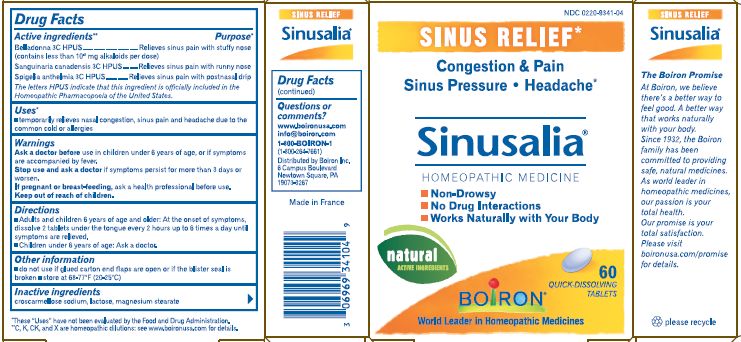 DRUG LABEL: Sinusalia
NDC: 0220-9341 | Form: TABLET
Manufacturer: Laboratoires Boiron
Category: homeopathic | Type: HUMAN OTC DRUG LABEL
Date: 20200227

ACTIVE INGREDIENTS: BELLADONNA LEAF 3 [hp_C]/1 1; SANGUINARIA CANADENSIS ROOT 3 [hp_C]/1 1; SPIGELIA MARILANDICA ROOT 3 [hp_C]/1 1
INACTIVE INGREDIENTS: CROSCARMELLOSE SODIUM; LACTOSE; MAGNESIUM STEARATE

Sinusalia

ACTIVE INGREDIENT

Belladonna 3C, Sanguinaria canadensis 3C, Spigelia anthelmia 3C

INDICATIONS AND USAGE

Temporary relieves nasal congestion and pain due to the common cold or allergies.

INACTIVE INGREDIENT

Croscarmellose sodium, lactose, magnesium stearate.

HOW SUPPLIED

60 tablets

PURPOSE

Belladonna 3C HPUS relieves sinus pain with stuffy nose
(contains less than 10^-8 mg alkaloids)
Sanguinaria canadensis 3C HPUS relieves sinus pain with runny nose
Spegelia anthelmia 3C HPUS relieves sinus pain with postnasal drip

STORAGE AND HANDLING

Store at 68-77o F (20-25o C)

Questions, Comments
www.boironusa.com
info@boironusa.com
1-800-BOIRON-1 (1-800-264-7661)
Boiron Information Center
6 campus Bouelvard
Newtown Square, PA
19073-3267

Ask a doctor before use in children younger than 6 years of age.
If symptoms are accompanied by fever.

Stop use and ask a doctor if symptoms persist continuously for more than 3 days or worsen.

Keep out of reach of children

PREGNANCY OR BREAST FEEDING

If pregnant or breast-feeding, ask a health professional before use.

Non drowsy, no drug interactions

Do not use if blister seal is broken

DOSAGE AND ADMINISTRATION

(adults and children 6 years of age and older)
Take 1 dose (2 tablets) every 2 hours up to 6 times a day.
Allow tablets to dissolve in the mouth.